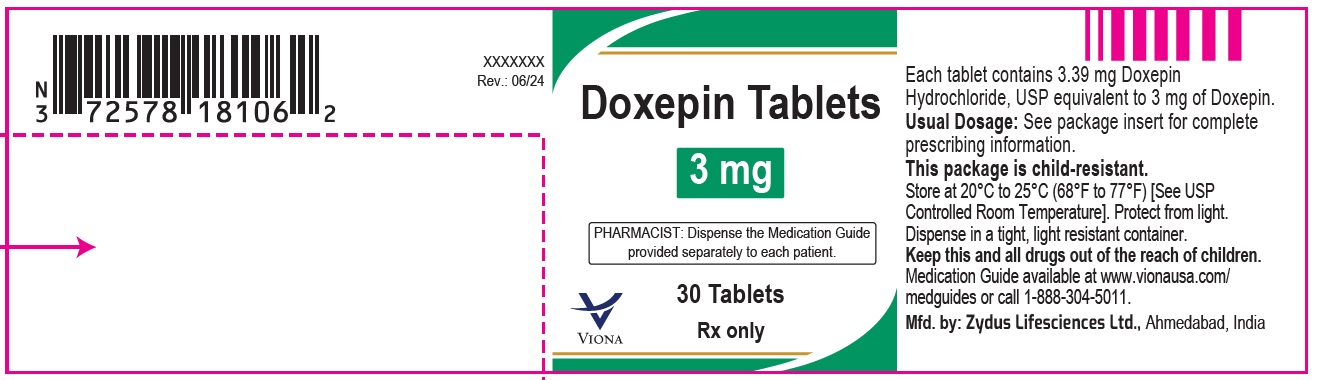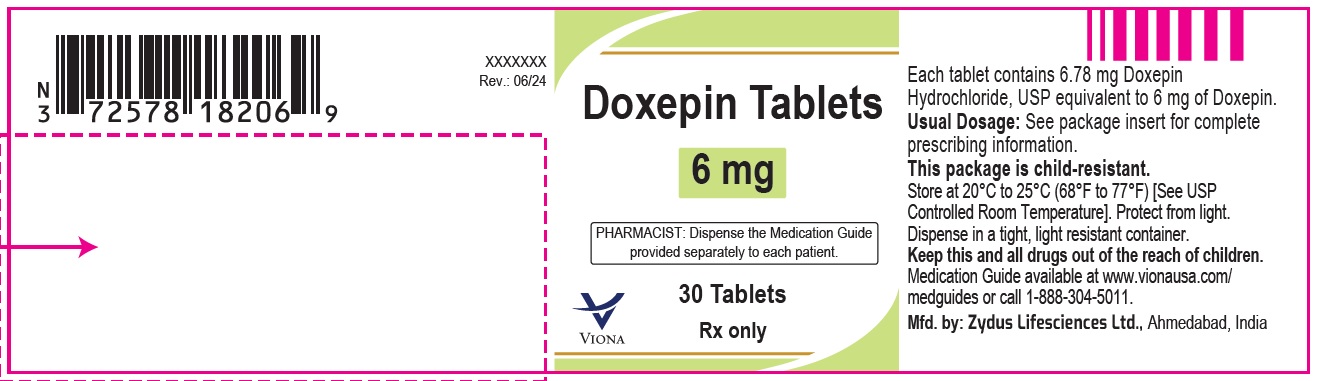 DRUG LABEL: doxepin
NDC: 70771-1528 | Form: TABLET
Manufacturer: Zydus Lifesciences Limited
Category: prescription | Type: HUMAN PRESCRIPTION DRUG LABEL
Date: 20250108

ACTIVE INGREDIENTS: DOXEPIN HYDROCHLORIDE 3 mg/1 1
INACTIVE INGREDIENTS: FD&C BLUE NO. 1; LACTOSE MONOHYDRATE; MAGNESIUM STEARATE; SODIUM STARCH GLYCOLATE TYPE A POTATO; STARCH, CORN; TALC

DOXEPIN tablets, for oral use

PACKAGE LABEL.PRINCIPAL DISPLAY PANEL

NDC 70771-1528-3 in bottle of 30 tablets

Doxepin Tablets, 3 mg

Rx only

30 tablets

NDC 70771-1529-3 in bottle of 30 tablets

Doxepin Tablets, 6 mg

Rx only

30 tablets